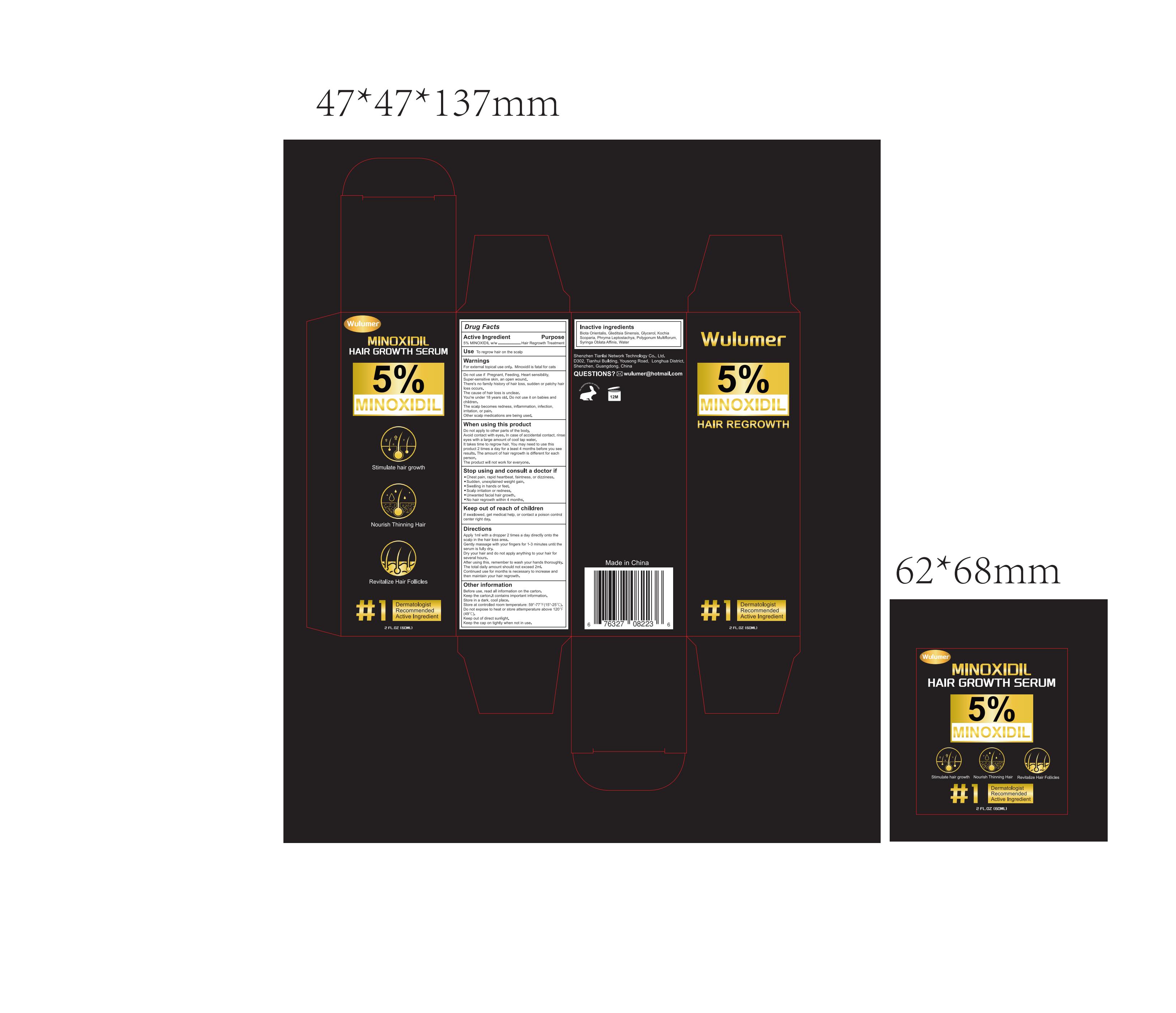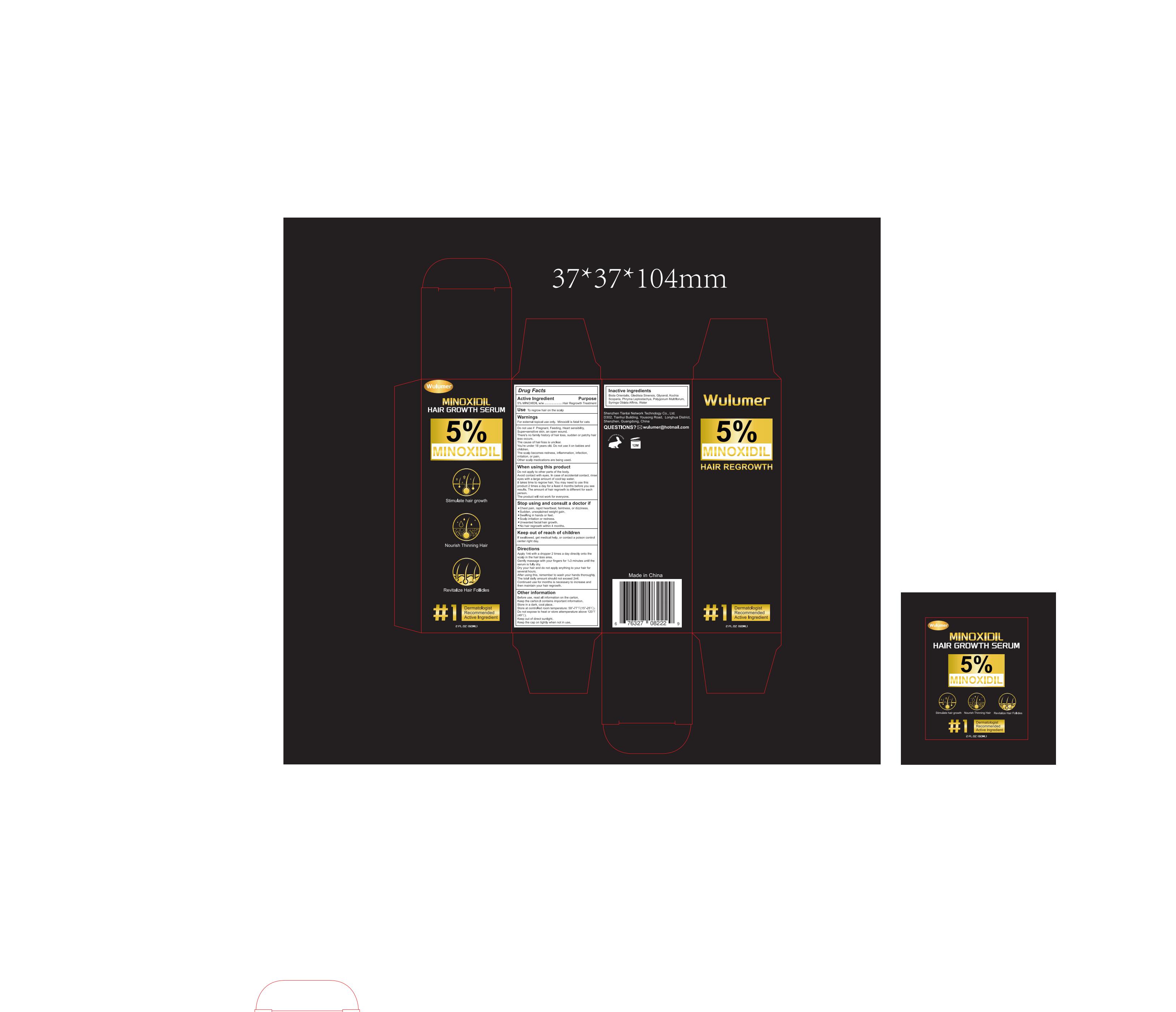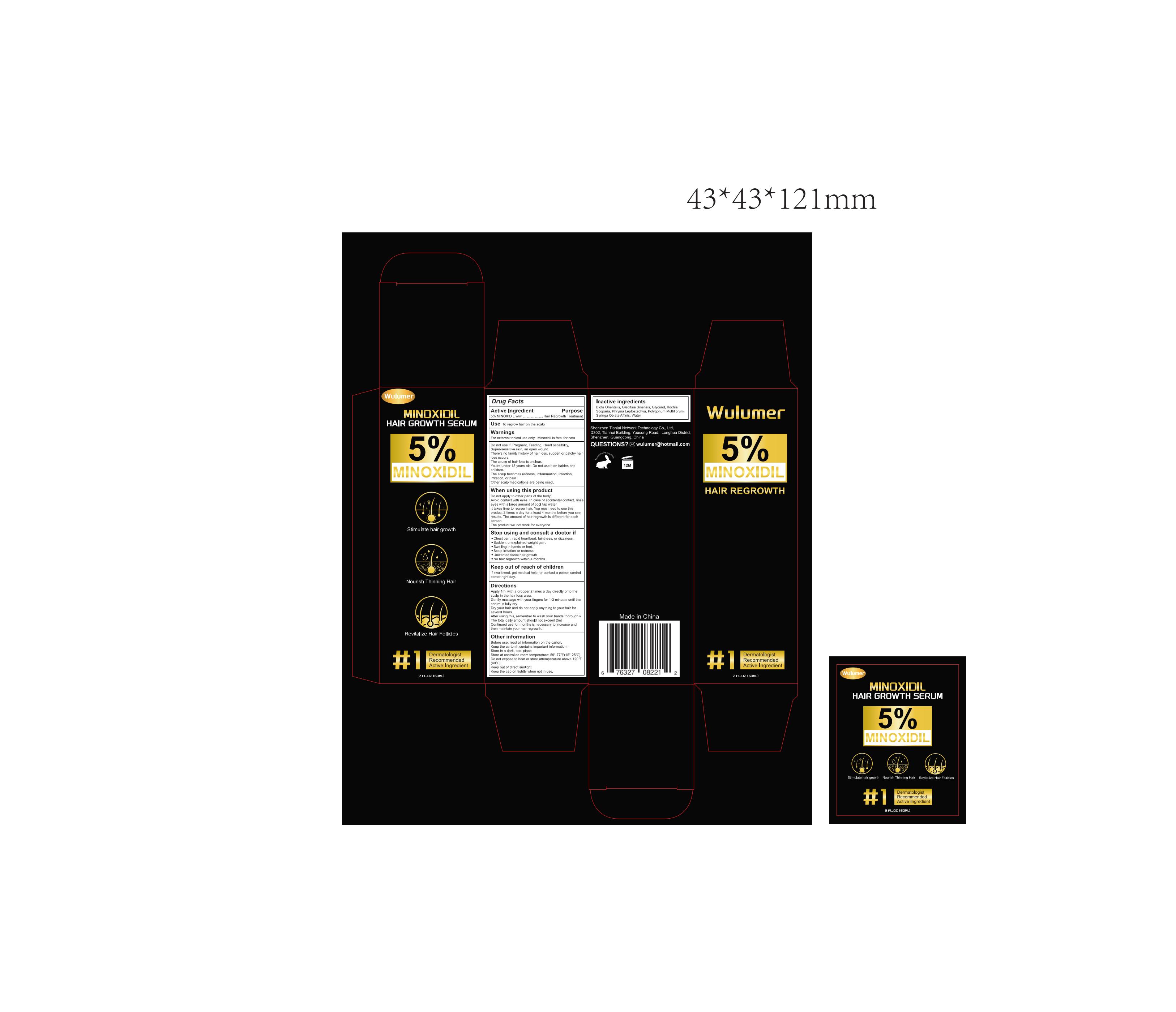 DRUG LABEL: Wulumer 5% Minoxidil Hair Rrowth Oil
NDC: 84049-001 | Form: LIQUID
Manufacturer: Shenzhen Tianlai Network Technology Co., Ltd.
Category: otc | Type: HUMAN OTC DRUG LABEL
Date: 20240123

ACTIVE INGREDIENTS: MINOXIDIL 5 g/100 mL
INACTIVE INGREDIENTS: PLATYCLADUS ORIENTALIS WHOLE; PHRYMA LEPTOSTACHYA WHOLE; WATER; BASSIA SCOPARIA WHOLE; GLEDITSIA SINENSIS WHOLE; GLYCERIN

84049-001

Active Ingredient

5% MINOXIDIL w/w

Purpose

Hair Regrowth Treatment

Use

To regrow hair on the scalp

Warnings

For external topical use only.
Minoxidil is fatal for cats.

Do not use

Pregnant, Feeding, Heart sensibility, Super-sensitive skin, an open wound.
There's no family history of hair loss, sudden or patchy hair loss occurs.
The cause of hair loss is unclear.
You're under 18 years old. Do not use it on babies and children.
The scalp becomes redness, inflammation, infection, irritation, or pain.
Other scalp medications are being used.

When Using

Do not apply to other parts of the body.
Avoid contact with eyes. In case of accidental contact, rinse eyes with a large amount of cool tap water.
It takes time to regrow hair, You may need to use this product 2 times a day for a least 4 months before you see results. The amount of hair regrowth is different for each person.
The product will not work for everyone.

Stop Use

Chest pain, rapid heartbeat, faintness, or dizziness.
Sudden, unexplained weight gain.
Swelling in hands or feet.
Scalp irritation or redness.
Unwanted facial hair growth.
No hair regrowth within 4 months.

Ask Doctor

Chest pain, rapid heartbeat, faintness, or dizziness.
Sudden, unexplained weight gain.
Swelling in hands or feet.
Scalp irritation or redness.
Unwanted facial hair growth.
No hair regrowth within 4 months.

Keep Oot Of Reach Of Children

Keep out of reach of children. If swallowed, get medical help, or contact a poison control center right day.

Directions

Apply 1ml with a dropper 2 times a day directly onto the scalp in the hair loss area.
Gently massage with your fingers for 1-3 minutes until the serum is fully dry.
Dry your hair and do not apply anything to your hair for several hours.
After using this, remember to wash your hands thoroughly.
The total daily amount should not exceed 2ml.
Continued use for months is necessary to increase and then maintain your hair regrowth.

Other information

Before use, read all information on the carton.
Keep the carton.lt contains important information.
Store in a dark, cool place.
Store at controlled room temperature: 59°-77℉(15°-25℃).
Do not expose to heat or store attemperature above 120℉(49℃).
Keep out of direct sunlight.
Keep the cap on tightly when not in use.

Inactive ingredients

Biota Orientalis, Gleditsia Sinensis, Glycerol, Kochia Scoparia, Phryma Leptostachya, Polygonum Multiflorum, Syringa Oblata Affinis, Water

Questions

wulumer@hotmail.com